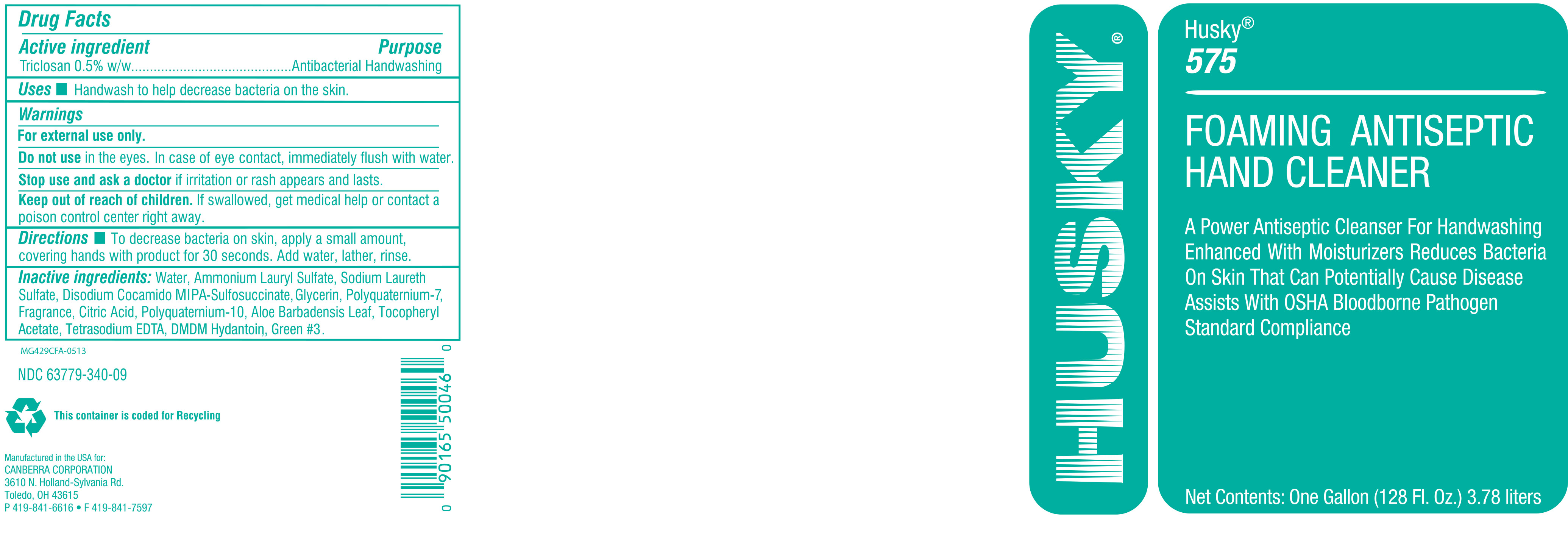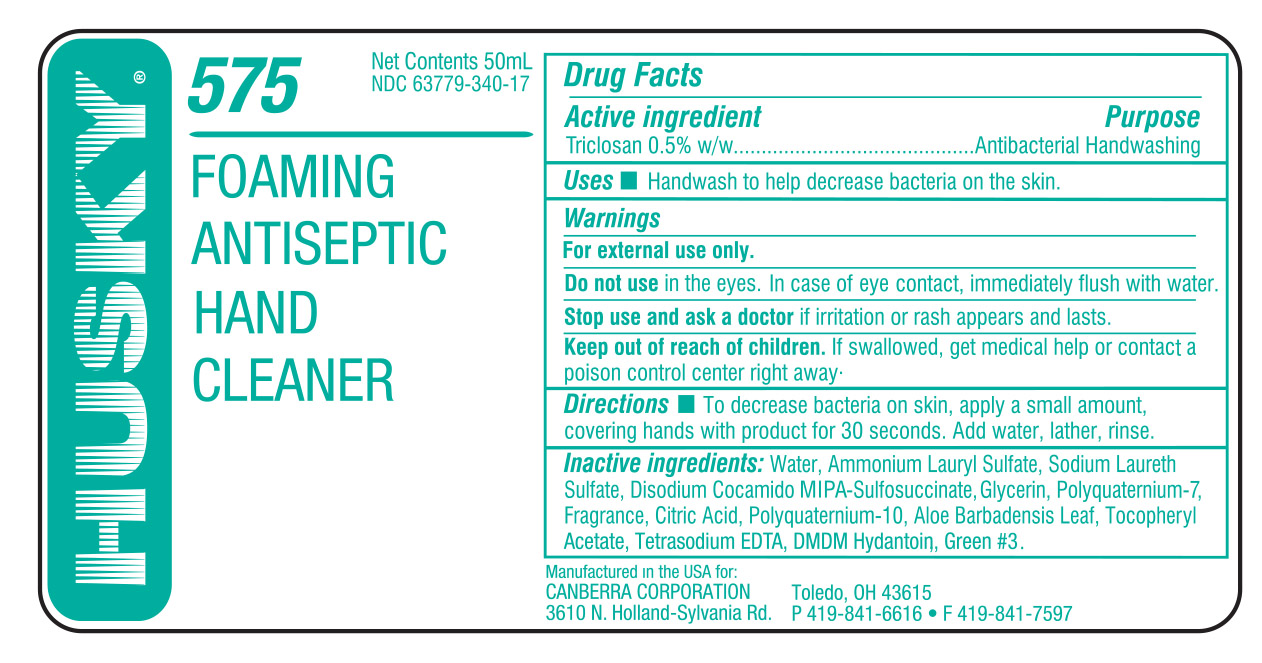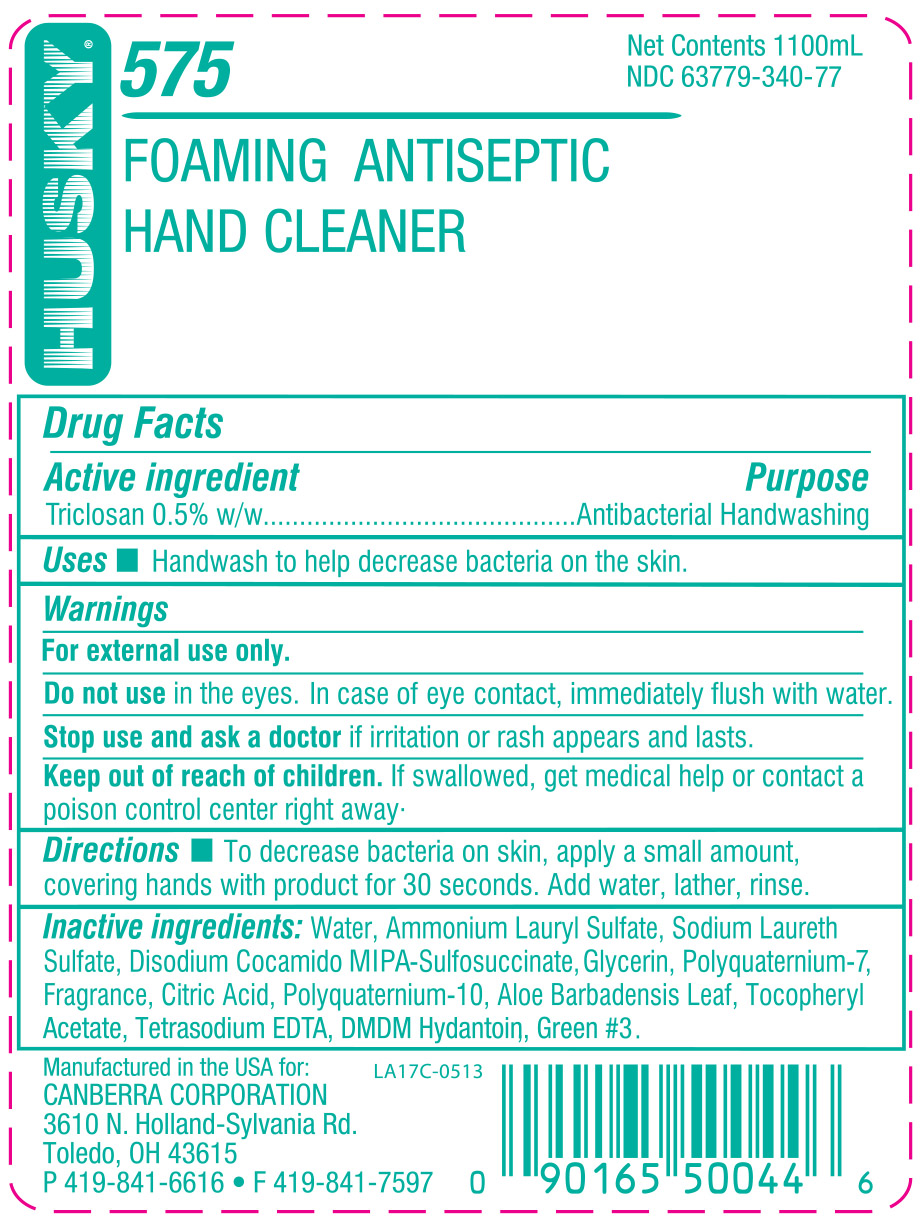 DRUG LABEL: Husky 575 Foaming Antiseptic Hand Cleaner
NDC: 63779-340 | Form: SOLUTION
Manufacturer: Canberra Corporation
Category: otc | Type: HUMAN OTC DRUG LABEL
Date: 20140103

ACTIVE INGREDIENTS: TRICLOSAN 20.8 g/100 mL
INACTIVE INGREDIENTS: WATER; POLYQUATERNIUM-10 (1000 MPA.S AT 2%); EDETATE SODIUM; AMMONIUM LAURYL SULFATE; SODIUM LAURETH SULFATE; GLYCERIN; POLYQUATERNIUM-7 (70/30 ACRYLAMIDE/DADMAC; 1600 KD); CITRIC ACID MONOHYDRATE; FD&C GREEN NO. 3; DMDM HYDANTOIN; ISOSTEARAMIDOPROPYL MORPHOLINE LACTATE; ALPHA-TOCOPHEROL ACETATE; ALOE VERA LEAF

Foaming Antiseptic Hand Cleaner

ACTIVE INGREDIENT

Triclosan 0.5% w/w.......Antibacterial Handwashing

INACTIVE INGREDIENT

Water, Ammonium Lauryl Sulfate, Sodium Laureth Sulfate, Disodium Cocamido MIPA-Sulfosuccinate, Glycerin, Polyquaternium-7, Fragrance, Citric Acid, Polyquaternium-10, Aloe Barbadensis Leaf, Tocopheryl Acetate, Tetrasodium EDTA, DMDM Hydantoin, Green #3.

PURPOSE

Handwash to help decrease bacteria on the skin.

WARNINGS

For external use only.

Do not use in the eyes. In case of eye contact, immediately flush with water.

Stop use and ask a doctor if irritation or rash appears and lasts.

Keep out of reach of children. If swallowed, get medical help or contact a poison control center right away.

DOSAGE AND ADMINISTRATION

To decrease bacteria on skin, apply a small amount, covering hands with product for 30 seconds. Add water, lather, rinse.

INDICATIONS AND USAGE

Handwash to help decrease bacteria on the skin.

Do not use in the eyes. In case of eye contact, immediately flush with water.

Stop use and ask a doctor if irritation or rash appears and lasts.

Keep out of reach of children. If swallowed, get medical help or contact a poison control center right away.

Keep out of reach of children. If swallowed, get medical help or contact a poison control center right away.

PACKAGE LABEL

63779-340-09.jpg

PACKAGE LABEL

63779-340-77.jpg

PACKAGE LABEL

63779-340-17.jpg